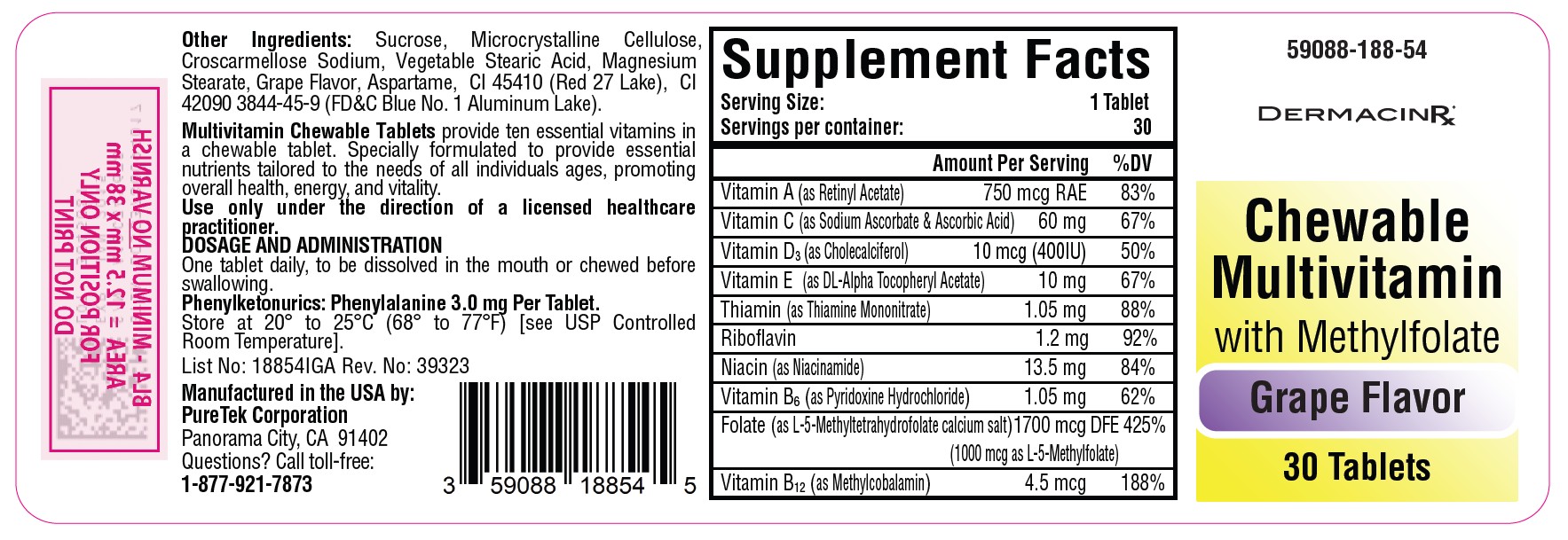 DRUG LABEL: Multivitamin Chewable with Methylfolate
NDC: 59088-188 | Form: TABLET, CHEWABLE
Manufacturer: PureTek Corporation
Category: other | Type: DIETARY SUPPLEMENT
Date: 20250827

ACTIVE INGREDIENTS: VITAMIN A 750 ug/1 1; ASCORBIC ACID 24 mg/1 1; SODIUM ASCORBATE 36 mg/1 1; CHOLECALCIFEROL 10 ug/1 1; .ALPHA.-TOCOPHEROL ACETATE, DL- 10 mg/1 1; PYRIDOXINE HYDROCHLORIDE 1.05 mg/1 1; THIAMINE MONONITRATE 1.05 mg/1 1; RIBOFLAVIN 1.2 mg/1 1; NIACIN 13.5 mg/1 1; LEVOMEFOLATE CALCIUM 1000 ug/1 1; METHYLCOBALAMIN 4.5 ug/1 1
INACTIVE INGREDIENTS: SUCROSE; CROSCARMELLOSE SODIUM; D&C RED NO. 27; FD&C BLUE NO. 1; MAGNESIUM STEARATE; CELLULOSE, MICROCRYSTALLINE; STEARIC ACID; ASPARTAME

NHRIC 59088-188-54
Multivitamin Chewable Tablets with Methylfolate

Each Chewable Tablet contains:

 | Amount Per Serving | % Daily Value
Vitamin A (as Retinyl Acetate) | 750 mcg RAE | 83%
Vitamin C (as Sodium Ascorbate & Ascorbic Acid) | 60mg | 67%
Vitamin D3 (as Cholecalciferol) | 10 mcg (400 IU) | 50%
Vitamin E (as DL-Alpha Tocopheryl Acetate) | 10 mg | 67%
Thiamin (as Thiamine Mononitrate) | 1.05 mg | 88%
Riboflavin | 1.2 mg | 92%
Niacin (as Niacinamide) | 13.5 mg | 84%
Vitamin B6 (as Pyridoxine Hydrochloride) | 1.05 mg | 62%
Folate (as L-5-Methyltetrahydrofolate calcium salt) | 1700 mcg DFE (1000 mcg as L-5-Methylfolate) | 425%
Vitamin B12 (as Methylcobalamin) | 4.5 mcg | 188%

Other Ingredients:

Sucrose, Microcrystalline Cellulose, Croscarmellose Sodium, Vegetable Stearic Acid, Magnesium Stearate, Grape Flavor, Aspartame, CI 45410 (Red 27 Lake), CI 42090 3844-45-9 (FD&C Blue No. 1 Aluminum Lake).

Phenylketonurics: Phenylalanine 3.0 mg Per Tablet.

INDICATIONS AND USAGE

Multivitamin Chewable Tablets with Methylfolate is indicated to provide significant amounts of Vitamins A, C, D, E, thiamine, riboflavin, niacin, vitamin B6, vitamin B12, and folate to supplement the diet, and to help assure that nutritional deficiencies of these vitamins will not develop.

This statement has not been evaluated by the Food and Drug Administration. This product is not intended to diagnose, treat, cure, or prevent any disease.

Contraindications:

This product is contraindicated in patients with known hypersensitivity to any of its ingredients.

WARNING

Keep out of the reach of children. In case of accidental overdose, seek professional assistance or contact a Poison Control Center immediately.

CAUTION: Should be chewed.

PRECAUTIONS

Folate in doses above 0.1 mg daily may obscure pernicious anemia, in that hematologic remission can occur while neurological manifestations remain progressive. There is a potential danger in administering folate to patients with undiagnosed anemia, since folate may obscure the diagnosis of pernicious anemia by alleviating the hematologic manifestations of the disease while allowing the
neurologic complications to progress. This may result in severe nervous system damage before the correct diagnosis is made.
Adequate doses of vitamin B12 may prevent, halt, or improve the neurologic changes caused by pernicious anemia.

The patient’s medical conditions and consumption of other drugs, herbs, and/or supplements should be considered.

Call your doctor about side effects. To report side effects, call PureTek Corporation at 1-877-921-7873 or FDA at 1-800-FDA-1088 or www.fda.gov/medwatch.

Adverse Reactions:

Folate: Allergic sensitizations has been reported following both oral and parenteral administration of folate. Adverse reactions have been reported with specific vitamins and minerals but generally at levels substantially higher than those contained herein. However, allergic and idiosyncratic reactions are possible at lower levels.

DOSAGE AND ADMINISTRATION

One tablet daily, to be dissolved in the mouth or chewed before swallowing.

HOW SUPPLIED

Multivitamin chewable tablets are light purple with speckles, grape flavor, un-scored, round tablets. Available in bottle of 30 tablets – NHRIC 59088-188-54. Dispense in a tight, light resistant container with a child resistant closure as defined in the USP/NF.

STORAGE

Do not use if bottle seal is broken.
KEEP THIS AND ALL MEDICATIONS OUT OF THE REACH OF CHILDREN.
Store at 20° to 25°C (68° to 77°F) [see USP Controlled Room Temperature].

Multivitamin Chewable Tablets with Methylfolate

HRIC 59088-188-54 *

Multivitamin Chewable Tablet with Methylfolate

30 tablets

Manufactured in the USA by:
PureTek Corporation
Panorama City, CA 91402
Questions? Call toll-free:
1-877-921-7873

*Does not represent these product codes to be National Drug Codes (NDC). Product codes are formatted according to standard industry practice, to meet the formatting requirement by pedigree reporting and supply-chain control including pharmacies.

† The most appropriate way to ensure pedigree reporting consistent with these regulatory guidelines and safety monitoring is to dispense this product by prescription. This is not an Orange Book product. This product may be administered only under a physician’s supervision and all prescriptions using this product shall be pursuant to state statutes as applicable. The ingredients, indication or claims of this product are not to be construed to be drug claims.